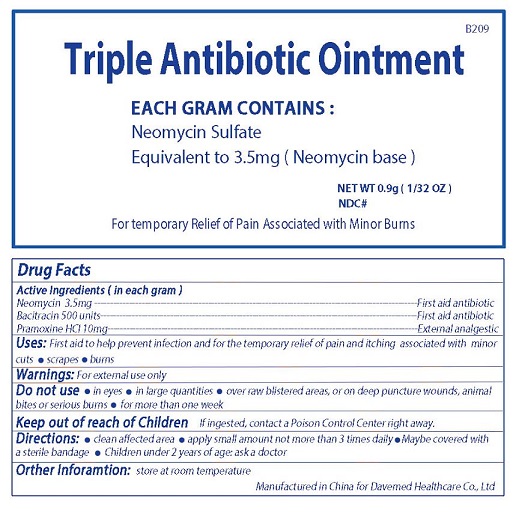 DRUG LABEL: Triple Antiobiotic
NDC: 70897-003 | Form: OINTMENT
Manufacturer: Davemed Healthcare Co., Ltd.
Category: otc | Type: HUMAN OTC DRUG LABEL
Date: 20190201

ACTIVE INGREDIENTS: POLYMYXIN B SULFATE 5000 [iU]/1 g; NEOMYCIN SULFATE 5 mg/1 g; BACITRACIN ZINC 400 [iU]/1 g
INACTIVE INGREDIENTS: PETROLATUM

Triple Antiobiotic

DIRECTIONS

- clean affected area
- apply small amount not more than 3 times daily
- maybe covered with a sterile bandage
- children under 2 years of age ask a doctor

USES

First aid to help prevent infection and for the temporary relief of pain and itching associated with minor cuts, scrapes and burns

WARNINGS

FOR EXTERNAL USE ONLY

KEEP OUT OF REACH OF CHILDREN

If ingested contact a poison control center right away.

ACTIVE INGREDIENT

NEOMYCIN

BACITRACIN

PRAMOXINE HCI

INACTIVE INGREDIENT

Petrolatum

PURPOSE

First Aid Antibiotic. For temporary relief of pain associated with minor burns.